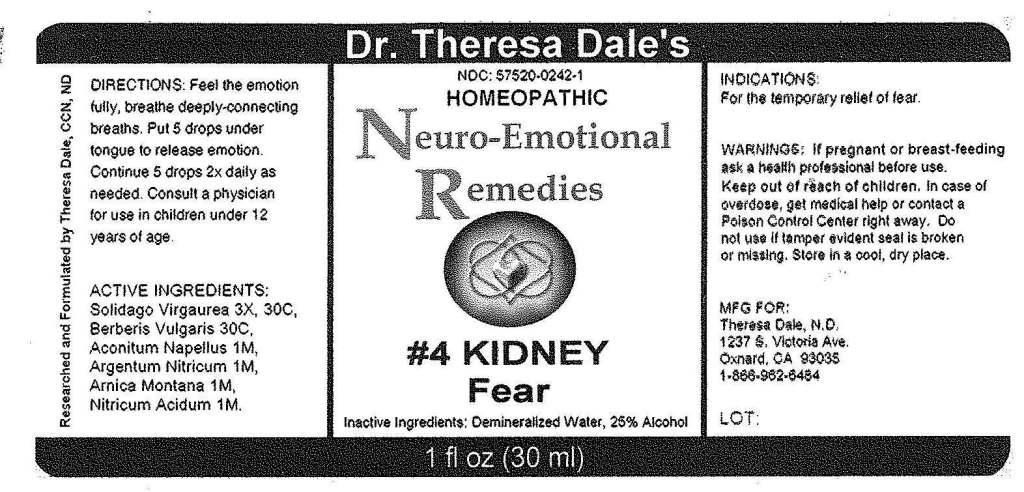 DRUG LABEL: 4 Kidney
NDC: 57520-0242 | Form: LIQUID
Manufacturer: Apotheca Company
Category: homeopathic | Type: HUMAN OTC DRUG LABEL
Date: 20100823

ACTIVE INGREDIENTS: SILVER NITRATE 1 [hp_M]/1 mL; ARNICA MONTANA 1 [hp_M]/1 mL; ACONITUM NAPELLUS 1 [hp_M]/1 mL; NITRIC ACID 1 [hp_M]/1 mL; BERBERIS VULGARIS ROOT BARK 30 [hp_C]/1 mL; SOLIDAGO VIRGAUREA FLOWERING TOP 30 [hp_C]/1 mL
INACTIVE INGREDIENTS: WATER; ALCOHOL

#4 Kidney

ACTIVE INGREDIENT

ACTIVE INGREDIENTS: Argentum nitricum 1M, Arnica montana 1M, Aconitum napellus 1M, Nitricum acidum 1M, Berberis vulgaris 30C, Solidago virgaurea 3X, 30C.

PURPOSE

INDICATIONS: For the temporary relief of fear.

WARNINGS

WARNINGS: If pregnant or breast-feeding, ask a health professional before use.

Keep out of reach of children. In case of overdose, get medical help or contact a Poison Control Center right away.

Do not use if tamper evident seal is broken or missing. Store in a cool, dry place.

DOSAGE AND ADMINISTRATION

DIRECTIONS: Feel the emotion fully, breathe deeply-connected breaths. Put 2 drops under tongue to release emotion. Continue 5 drops 2x daily as needed. Consult a physician for use in children under 12 years of age.

INACTIVE INGREDIENTS: Demineralized water, 25% Alcohol.

KEEP OUT OF REACH OF CHILDREN: In case of overdose, get medical help or contact a Poison Control Center right away.

INDICATIONS: For the temporary relief of fear.

QUESTIONS

MFG. FOR:

Theresa Dale, N.D.

1237 X Victoria Ave.

Oxnard, CA 93035

1-866-962-6434

PACKAGE LABEL

Dr. Theresa Dale's

NDC: 57520-0242-1

HOMEOPATHIC

Neuro-Emotional Remedies

#4 KIDNEY

Fear

1 fl oz (30 ml)